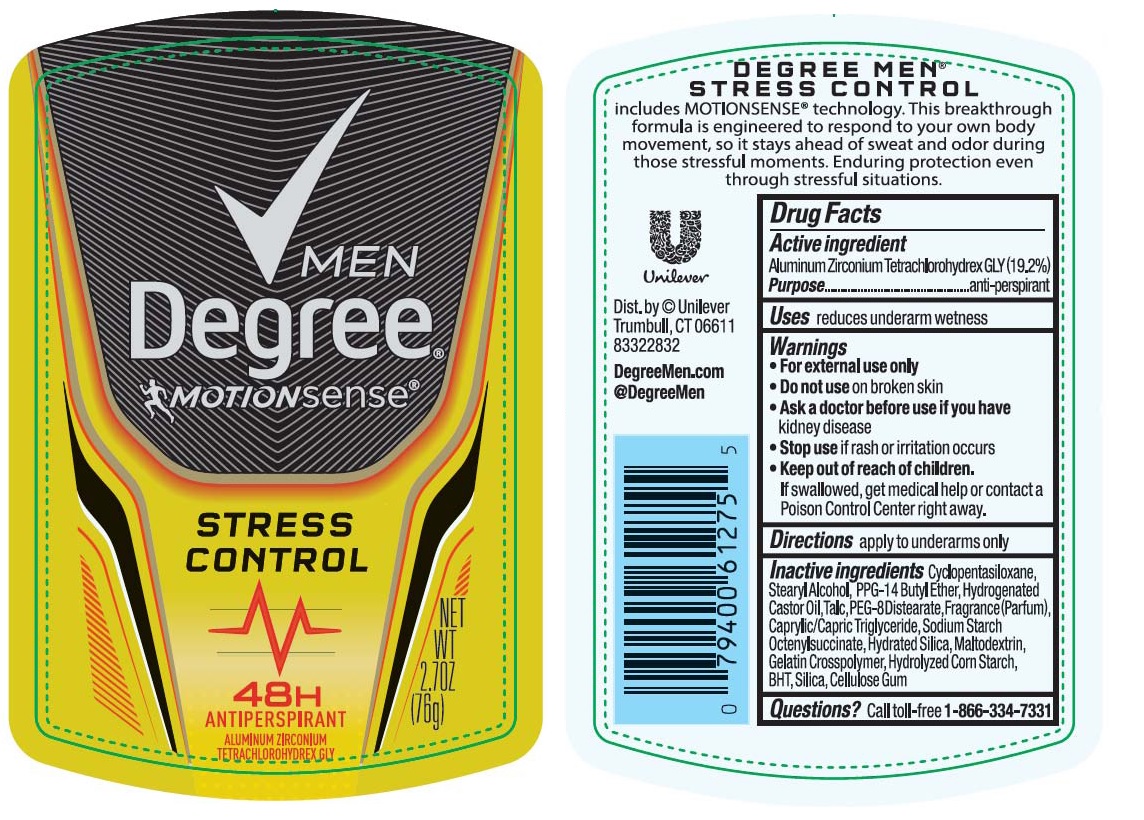 DRUG LABEL: Degree Men
NDC: 64942-1480 | Form: STICK
Manufacturer: Conopco, Inc. d/b/a/ Unilever
Category: otc | Type: HUMAN OTC DRUG LABEL
Date: 20161025

ACTIVE INGREDIENTS: ALUMINUM ZIRCONIUM TETRACHLOROHYDREX GLY 19.2 g/100 g
INACTIVE INGREDIENTS: CYCLOMETHICONE 5; STEARYL ALCOHOL; PPG-14 BUTYL ETHER; HYDROGENATED CASTOR OIL; TALC; PEG-8 DISTEARATE; MEDIUM-CHAIN TRIGLYCERIDES; HYDRATED SILICA; MALTODEXTRIN; STARCH, CORN; BUTYLATED HYDROXYTOLUENE; SILICON DIOXIDE; CARBOXYMETHYLCELLULOSE SODIUM, UNSPECIFIED FORM

Degree Men Motionsense Stress Control 48H Antiperspirant

Active ingredient

Aluminum Zirconium Tetrachlorohydrex GLY (19.2%)

Purpose

anti-perspirant

Uses

reduces underarm wetness

Warnings

- For external use only.
- Do not use on broken skin.
- Ask a doctor before use if you have kidney disease.
- Stop use if rash or irritation occurs.

Keep out of reach of children. If swallowed, get medical help or contact a Poison Control Center right away.

Directions

apply to underarms only

Inactive ingredients

Cyclopentasiloxane, Stearyl Alcohol, PPG-14 Butyl Ether, Hydrogenated Castor Oil, Talc, PEG-8 Distearate, Fragrance (Parfum), Caprylic/Capric Triglyceride, Sodium Starch Octerylsuccinate, Hydrated Silica, Maltodextrin, Gelatin Crosspolymer, Hydrolyzed Corn Starch, BHT, Silica, Cellulose Gum.

Questions?

Call toll-free 1-866-334-7331

DEGREE MEN STRESS CONTROL

includes MOTIONSENSE® technology. This breakthrough formula is engineered to respond to your own body movement, so it stays ahead of sweat and odor during those stressful moments. Enduring protection even through stressful situations.